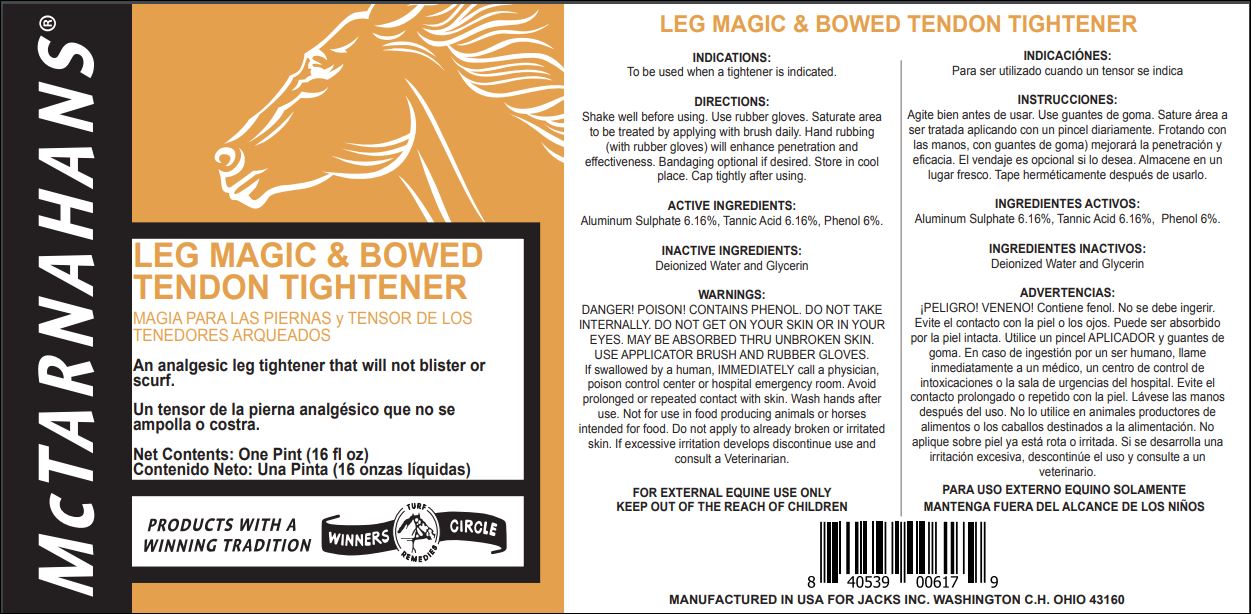 DRUG LABEL: LEG MAGIC
NDC: 61156-114 | Form: LINIMENT
Manufacturer: JACKS MFG INC
Category: animal | Type: OTC ANIMAL DRUG LABEL
Date: 20211208

ACTIVE INGREDIENTS: ALUMINUM SULFATE 0.0616 g/1 mL; TANNIC ACID 0.0616 g/1 mL; PHENOL 0.06 g/1 mL
INACTIVE INGREDIENTS: WATER 0.14167 mL/1 mL; GLYCERIN 0.01050 g/1 mL

LEG MAGIC & BOWED TENDON TIGHTENER

INDICATIONS

To be used when a tightener is indicated.

DIRECTIONS

Shake well before using.

Use rubber gloves.

Saturate area to be treated by applying with brush daily.

Hand rubbing (with rubber gloves) will enhance penetration and effectiveness.

Bandaging optional if desired.

Store in cool place.

Cap tightly after using.

WARNING

DANGER! POISON! CONTAINS PHENOL.
DO NOT TAKE INTERNALLY.
DO NOT GET ON YOUR SKIN OR IN YOUR EYES.
MAY BE ABSORBED THRU UNBROKEN SKIN.
USE APPLICATOR BRUSH AND RUBBER GLOVES

If swallowed by a human, IMMEDIATELY call a physician, poison control center or hospital emergency room.
Avoid prolonged or repeated contact with skin.
Wash hands after use.
Not for use in food producing animals or horses intended for food.
Do not apply to already broken or irritated skin.
If excessive irritation develops discontinue use and consult a Veterinarian.

FOR EXTERNAL EQUINE USE ONLY

KEEP OUT OF THE REACH OF CHILDREN